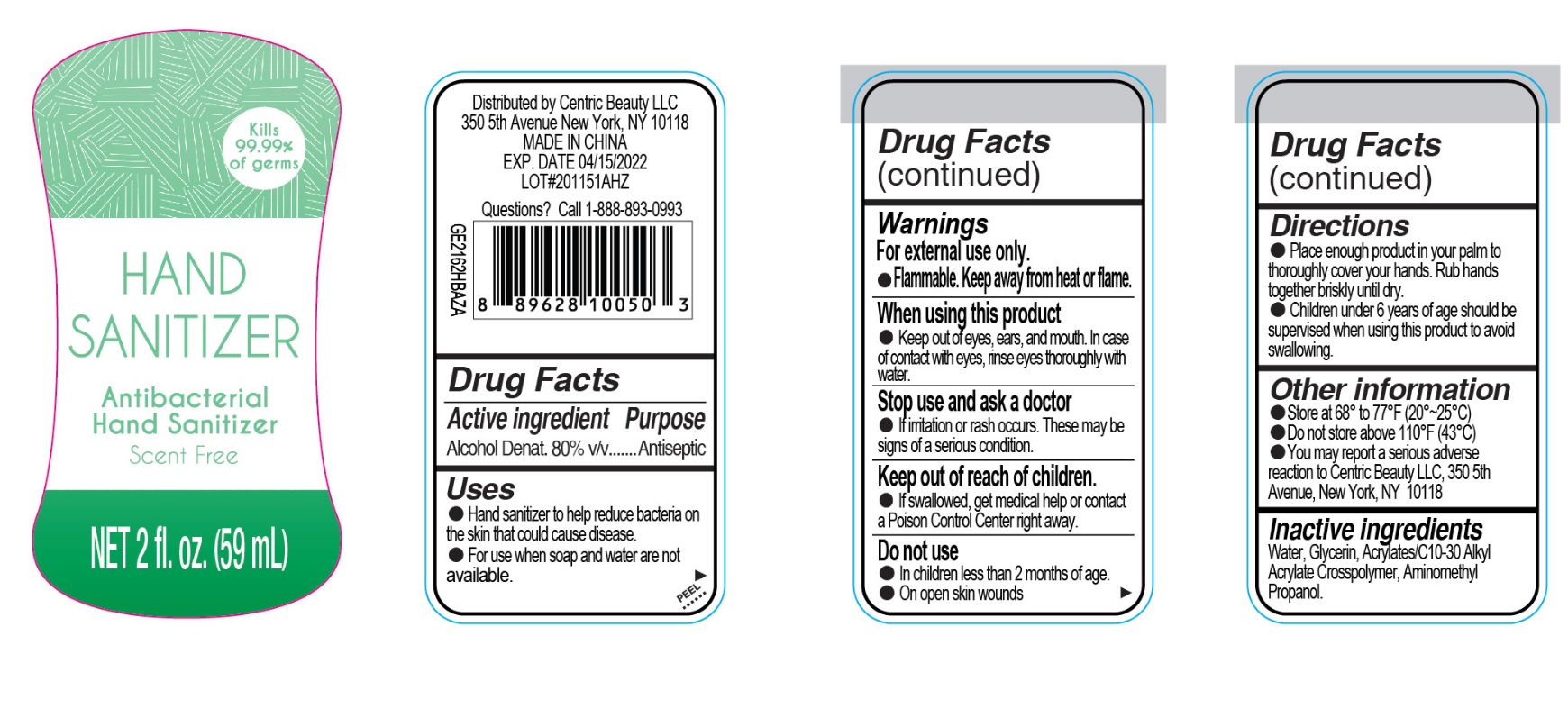 DRUG LABEL: Hand Sanitizer
NDC: 74395-001 | Form: GEL
Manufacturer: Centric Beauty LLC
Category: otc | Type: HUMAN OTC DRUG LABEL
Date: 20200406

ACTIVE INGREDIENTS: ALCOHOL 80 mL/100 mL
INACTIVE INGREDIENTS: WATER; AMINOMETHYLPROPANOL; GLYCERIN; CARBOMER INTERPOLYMER TYPE B (ALLYL PENTAERYTHRITOL CROSSLINKED)

Centric Beauty Hand Sanitizer

Active ingredient

Alcohol Denat. 80% v/v

Purpose

Antiseptic

Use

- Hand sanitizer to help reduce bacteria on the skin that could cause disease. For use when soap and water are not available.

Warnings

For external use only. Flammable. Keep away from heat or flame.

When using this product

keep out of eyes, ears, and mouth. In case of contact with eyes, rinse eyes thoroughly with water.

Stop use and ask a doctor

if irritation or rash occurs. These may be signs of a serious condition.

Keep out of reach of children.

If swallowed, get medical help or contact a Poison Control Center right away.

Do not use

- in children less than 2 months of age.
- on open skin wounds.

Directions

- Place enough product in your palm to thoroughly cover your hands. Rub hands together briskly until dry.
- Children under 6 years of age should be supervised when using this product to avoid swallowing.

Other information

- Store at 68 to 77F (20-25C)
- Do not store above 110F (43C)
- You may report a serious adverse reaction to Centric Beauty LLC, 350 5th Avenue, New York, NY 10118

Inactive ingredients

Water, Glycerin, Acrylates/C10-30 Alkyl Acrylate Crosspolymer, Aminomethyl Propanol.

Company Information

Distributed by

Centric Beauty LLC

350 5th Avenue

New York, NY 10118

MADE IN CHINA

Product Packaging - 59 mL bottle

Kills 99.9% of germs

HAND SANITIZER

Antibacterial Hand Sanitizer

Scent Free

NET 2 fl. oz. (59 mL)